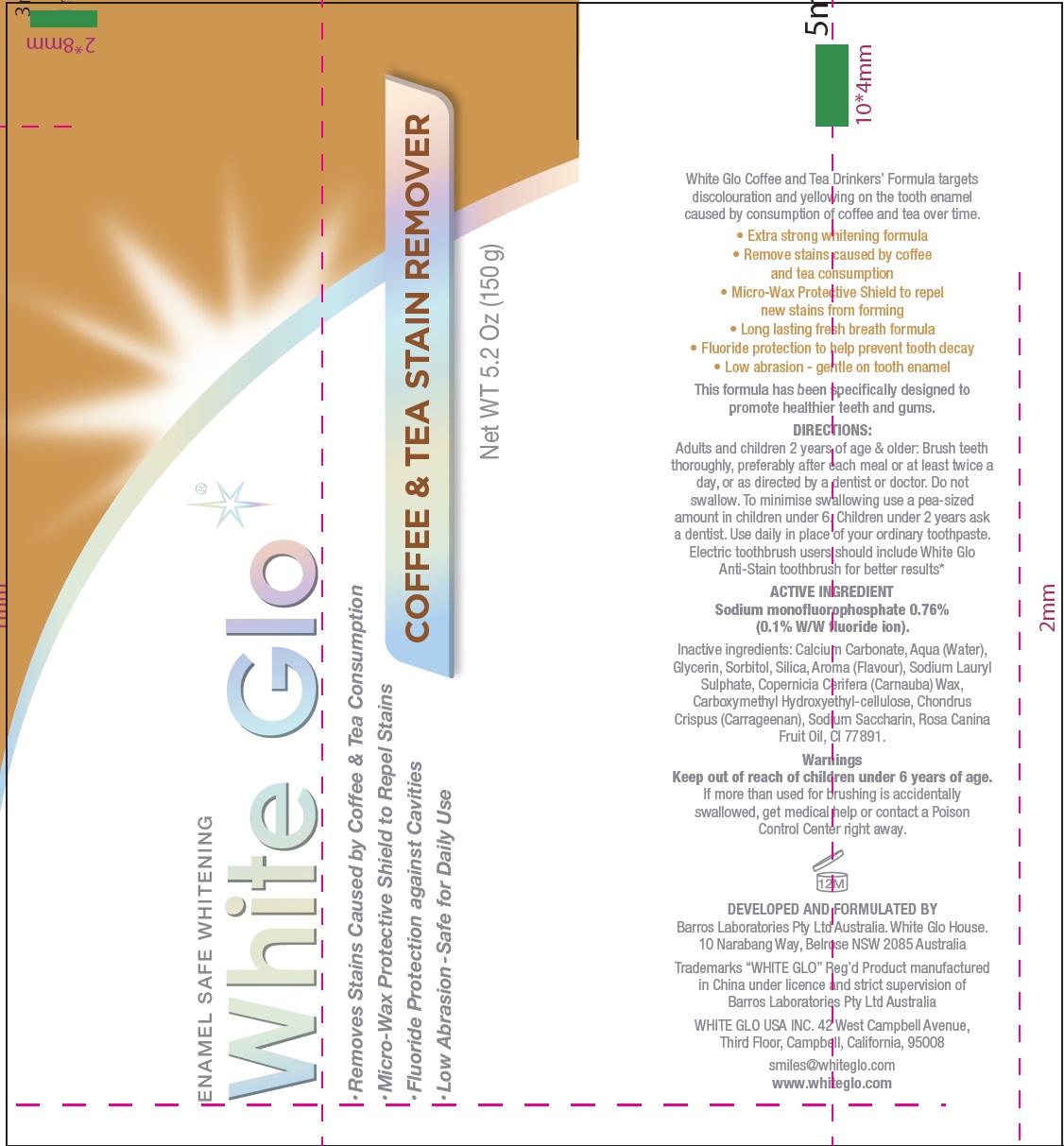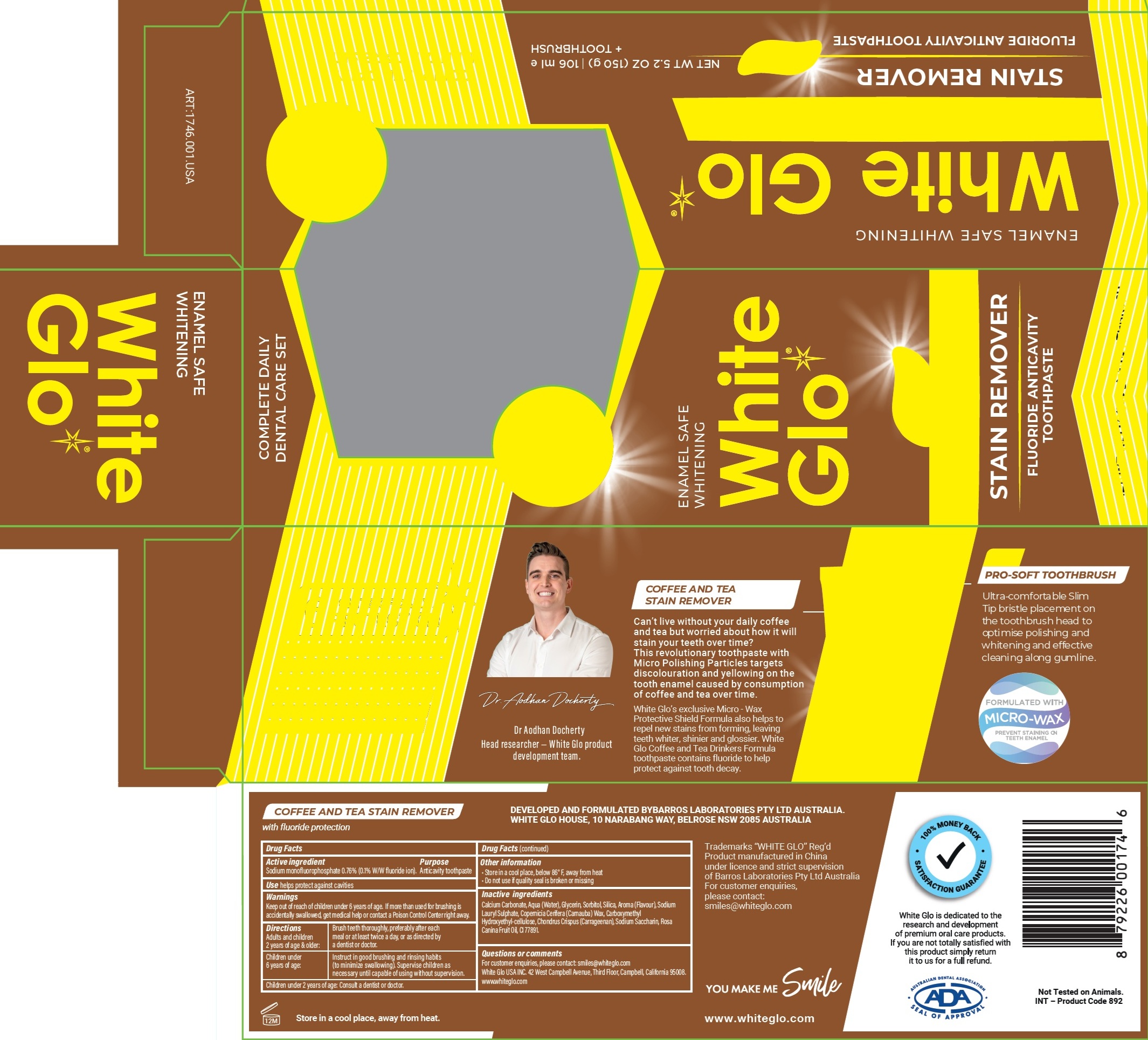 DRUG LABEL: White Glo Coffee and Tea Stain Remover Fluoride Anticavity
NDC: 73656-030 | Form: KIT | Route: DENTAL
Manufacturer: WHITE GLO USA INC
Category: otc | Type: HUMAN OTC DRUG LABEL
Date: 20250226

ACTIVE INGREDIENTS: SODIUM MONOFLUOROPHOSPHATE 7.6 mg/1 g
INACTIVE INGREDIENTS: CALCIUM CARBONATE; WATER; GLYCERIN; SORBITOL; SILICON DIOXIDE; SODIUM LAURYL SULFATE; CARNAUBA WAX; CHONDRUS CRISPUS; SACCHARIN SODIUM; ROSA CANINA FRUIT OIL; TITANIUM DIOXIDE

White Glo Coffee and Tea Stain Remover Fluoride Anticavity Toothpaste, and Toothbrush

Active ingredient

Sodium monofluorophosphate 0.76% (0.1% W/W fluoride ion).

Purpose

Anticavity toothpaste

Use

helps protect against cavities

Warnings

Keep out of reach of children under 6 years of age.

If more than used for brushing is accidentally swallowed, get medical help or contact a Poison Control Center right away.

Directions

Adults and children 2 years of age & older: | Brush teeth thoroughly, preferably after each meal or at least twice a day, or as directed by a dentist or doctor.
Children under 6 years of age: | Instruct in good brushing and rinsing habits (to minimize swallowing). Supervise children as necessary until capable of using without supervision.

Children under 2 years of age: Consult a dentist or doctor.

Other information

- Store in a cool place, below 86° F, away from heat
- Do not use if quality seal is broken or missing

Inactive ingredients

Calcium Carbonate, Aqua (Water), Glycerin, Sorbitol, Silica, Aroma (Flavour), Sodium Lauryl Sulphate, Copernicia Cerifera (Carnauba) Wax, Carboxymethyl Hydroxyethyl-cellulose, Chondrus Crispus (Carrageenan), Sodium Saccharin, Rosa Canina Fruit Oil, CI 77891.

Questions or comments

For customer enquiries, please contact: smiles@whiteglo.com www.whiteglo.com